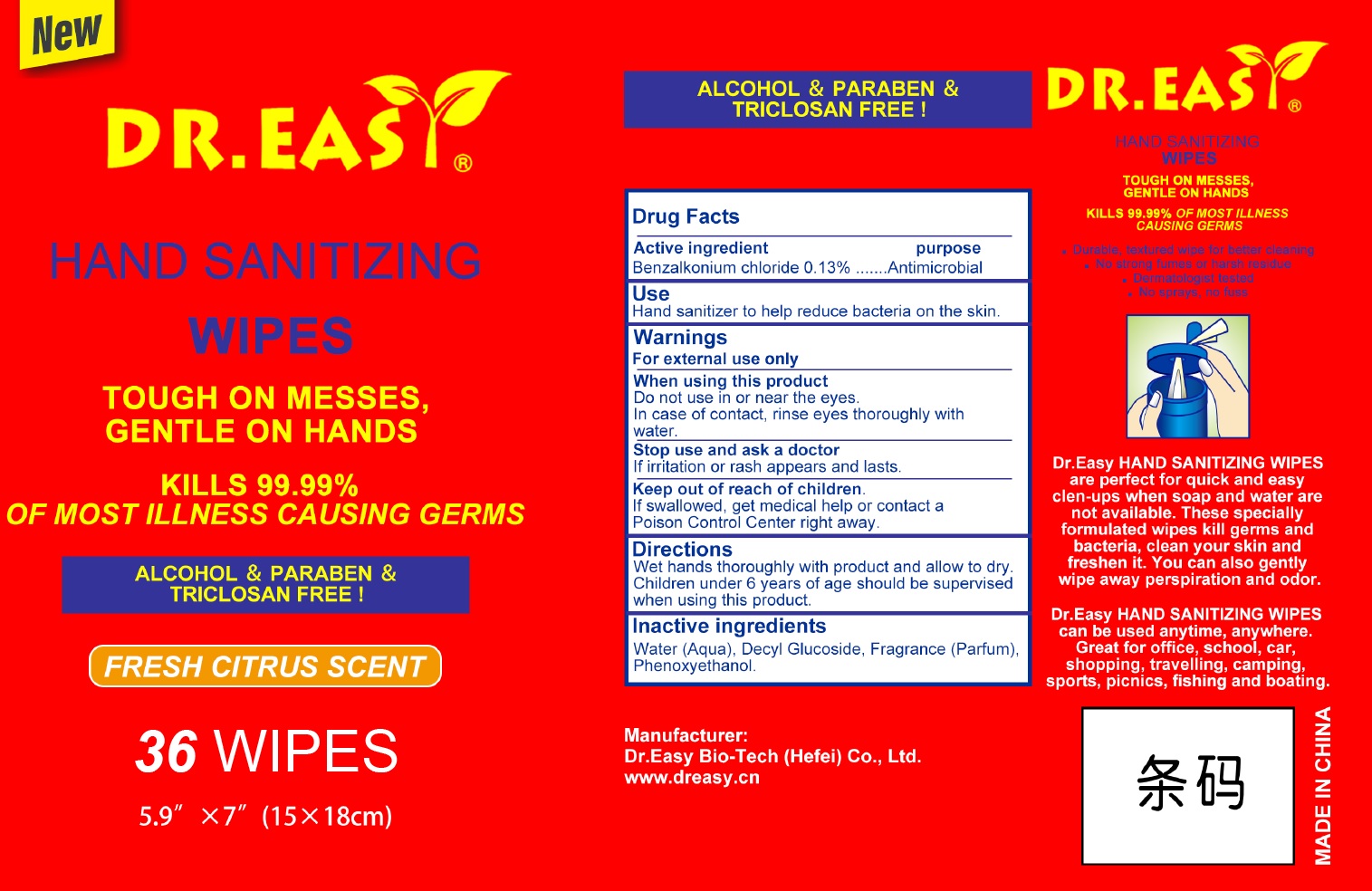 DRUG LABEL: Dr. Easy Hand Sanitizing Wipes
NDC: 52056-001 | Form: CLOTH
Manufacturer: Dr. Easy Bio-Tech (Hefei) Co., Ltd.
Category: otc | Type: HUMAN OTC DRUG LABEL
Date: 20200902

ACTIVE INGREDIENTS: BENZALKONIUM CHLORIDE 1.3 mg/1 mL
INACTIVE INGREDIENTS: WATER; DECYL GLUCOSIDE; PHENOXYETHANOL

Dr. Easy Hand Sanitizing Wipes

Active ingredient

Benzalkonium chloride 0.13%

purpose

Antimicrobial

Use

Hand sanitizer to help reduce bacteria on the skin.

Warnings:

For external use only

When using this product

Do not use in or near the eyes. In case of contact, rinse eyes thoroughly with water.

Stop use and ask a doctor

If irritation or rash appears and lasts.

Keep out of reach of children.

If swallowed, get medical help or contact a Poison Control Center right away.

Directions

Wet hands thoroughly with product and allow to dry. Children under 6 years of age should be supervised when using this product.

Inactive ingredients

Water (Aqua), Decyl Glucoside, Fragrance (Parfum), Phenoxyethanol.